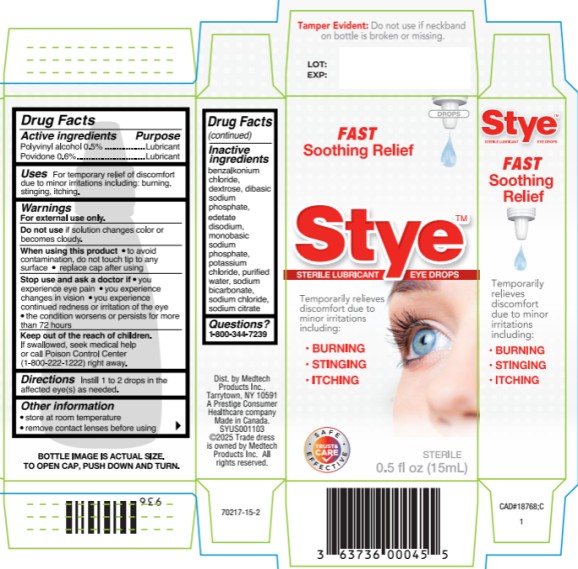 DRUG LABEL: Stye
NDC: 63029-324 | Form: SOLUTION/ DROPS
Manufacturer: Medtech Products Inc.
Category: otc | Type: HUMAN OTC DRUG LABEL
Date: 20251023

ACTIVE INGREDIENTS: POLYVINYL ALCOHOL, UNSPECIFIED 5 mg/1 mL; POVIDONE 6 mg/1 mL
INACTIVE INGREDIENTS: BENZALKONIUM CHLORIDE; DEXTROSE; SODIUM PHOSPHATE, DIBASIC; EDETATE DISODIUM; SODIUM PHOSPHATE, MONOBASIC; POTASSIUM CHLORIDE; SODIUM BICARBONATE; SODIUM CHLORIDE; SODIUM CITRATE; WATER

Stye Eye Drops 63029-324

Drug Facts

Active ingredients

Polyvinyl alcohol 0.5%
Povidone 0.6%

Purpose

Lubricant
Lubricant

Uses

For temporary relief of discomfort due to minor irritations including: burning, stinging, itching.

Warnings

for external use only

Do not use

if solution changes color or becomes cloudy

When using this product

- to avoid contamination, do not touch tip to any surface
- replace cap after using

Stop use and ask a doctor if

- you experience eye pain
- you experience changes in vision
- you experience continued redness or irritation of the eye
- the condition worsens or persists for more than 72 hours

Keep out of reach of children.

If swallowed, get medical help or contact a Poison Control Center (1-800-222-1222) right away

Directions

instill 1 to 2 drops in the affected eye(s) as needed

Other information

- store at room temperature
- remove contact lenses before using

Inactive ingredients

benzalkonium chloride, dextrose, dibasic sodium phosphate, edetate disodium, monobasic sodium phosphate, potassium chloride, purified water, sodium bicarbonate, sodium chloride, sodium citrate

Questions?

1-800-344-7239

PRINCIPAL DISPLAY PANEL

Stye ™

LUBRICANT EYE DROPS

STERILE 0.5 fl oz (15 mL)